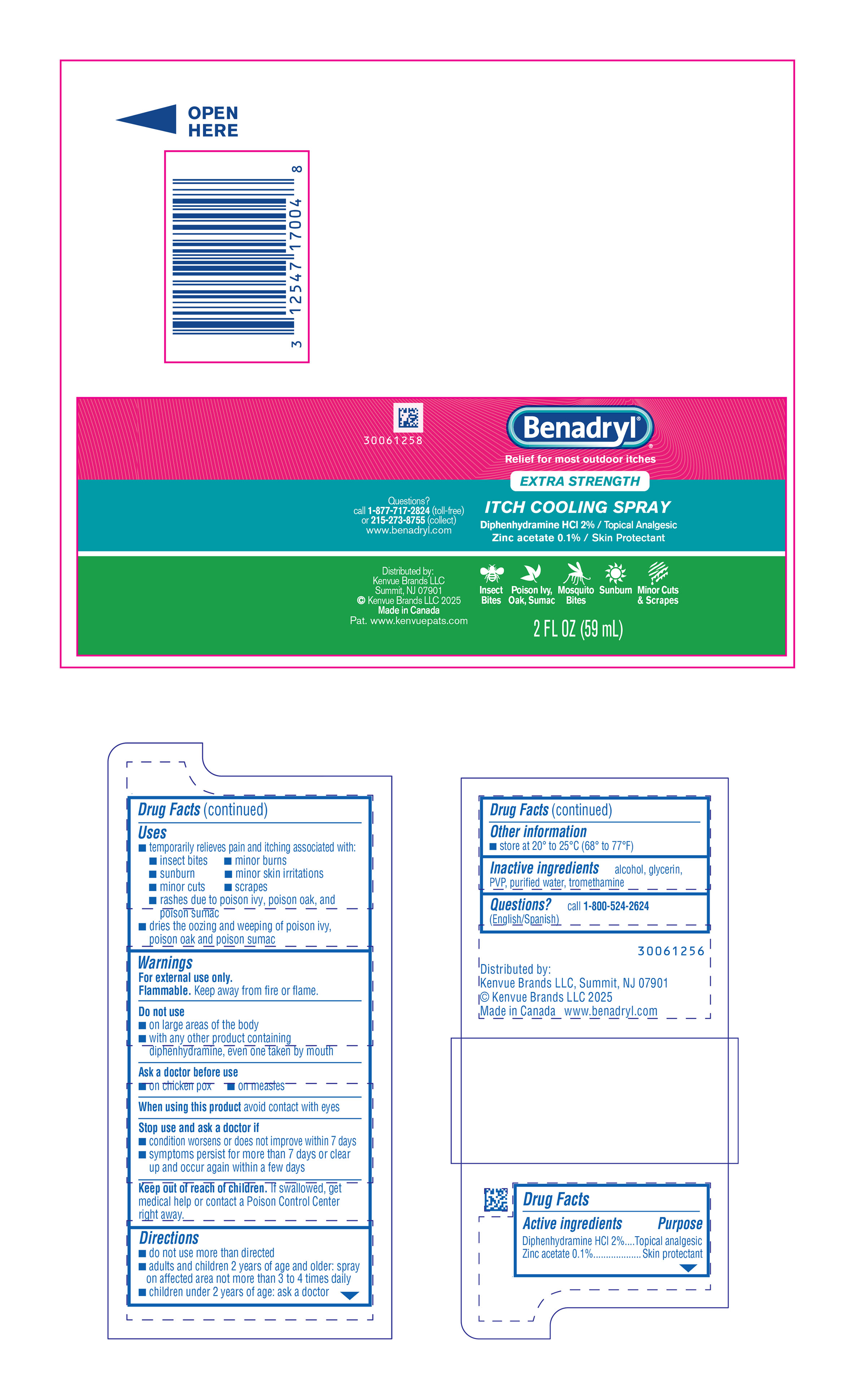 DRUG LABEL: Benadryl Extra Strength Itch Cooling
NDC: 69968-0270 | Form: SPRAY
Manufacturer: Kenvue Brands LLC
Category: otc | Type: HUMAN OTC DRUG LABEL
Date: 20250718

ACTIVE INGREDIENTS: DIPHENHYDRAMINE HYDROCHLORIDE 20 mg/1 mL; ZINC ACETATE 1 mg/1 mL
INACTIVE INGREDIENTS: ALCOHOL; GLYCERIN; POVIDONE, UNSPECIFIED; WATER; TROMETHAMINE

Benadryl® EXTRA STRENGTH ITCH COOLING SPRAY

Drug Facts

ACTIVE INGREDIENT

Active ingredients | Purpose
Diphenhydramine HCl 2% | Topical analgesic
Zinc acetate 0.1% | Skin protectant

Uses

- temporarily relieves pain and itching associated with:
  - insect bites
  - minor burns
  - sunburn
  - minor skin irritations
  - minor cuts
  - scrapes
  - rashes due to poison ivy, poison oak, and poison sumac
  - dries the oozing and weeping of poison ivy, poison oak and poison sumac

Warnings

For external use only.

Flammable. Keep away from fire or flame.

Do not use

- on large areas of the body
- with any other product containing diphenhydramine, even one taken by mouth

Ask a doctor before use

- on chicken pox
- on measles

When using this product avoid contact with eyes

Stop use and ask a doctor if

- condition worsens or does not improve within 7 days
- symptoms persist for more than 7 days or clear up and occur again within a few days

Keep out of reach of children. If swallowed, get medical help or contact a Poison Control Center right away.

Directions

- do not use more than directed
- adults and children 2 years of age and older: spray on affected area not more than 3 to 4 times daily
- children under 2 years of age: ask a doctor

Other information

- store at 20° to 25° C (68° to 77° F)

Inactive ingredients

alcohol, glycerin, PVP, purified water, tromethamine

Questions?

call 1-800-524-2624 (English/Spanish)

Distributed by:

Kenvue Brands LLC

Summit, NJ 07901

PRINCIPAL DISPLAY PANEL - 59 mL Bottle Label

Benadryl®

Relief for most outdoor itches

EXTRA STRENGTH

ITCH COOLING SPRAY

Diphenhydramine HCl 2% / Topical Analgesic

Zinc acetate 0.1 % / Skin Protectant

Questions?

call 1-877-717-2824 (toll-free)

or 215-273-8755 (collect)

www.benadryl.com

Insect Bites | Poison Ivy, Oak, Sumac | Mosquito Bites | Sunburn | Minor Cuts & Scrapes

Distributed by:

Kenvue Brands LLC
Summit, NJ 07901

© Kenvue Brands LLC 2025

Made in Canada

Pat. www.kenvuepats.com

2 FL OZ (59 mL)